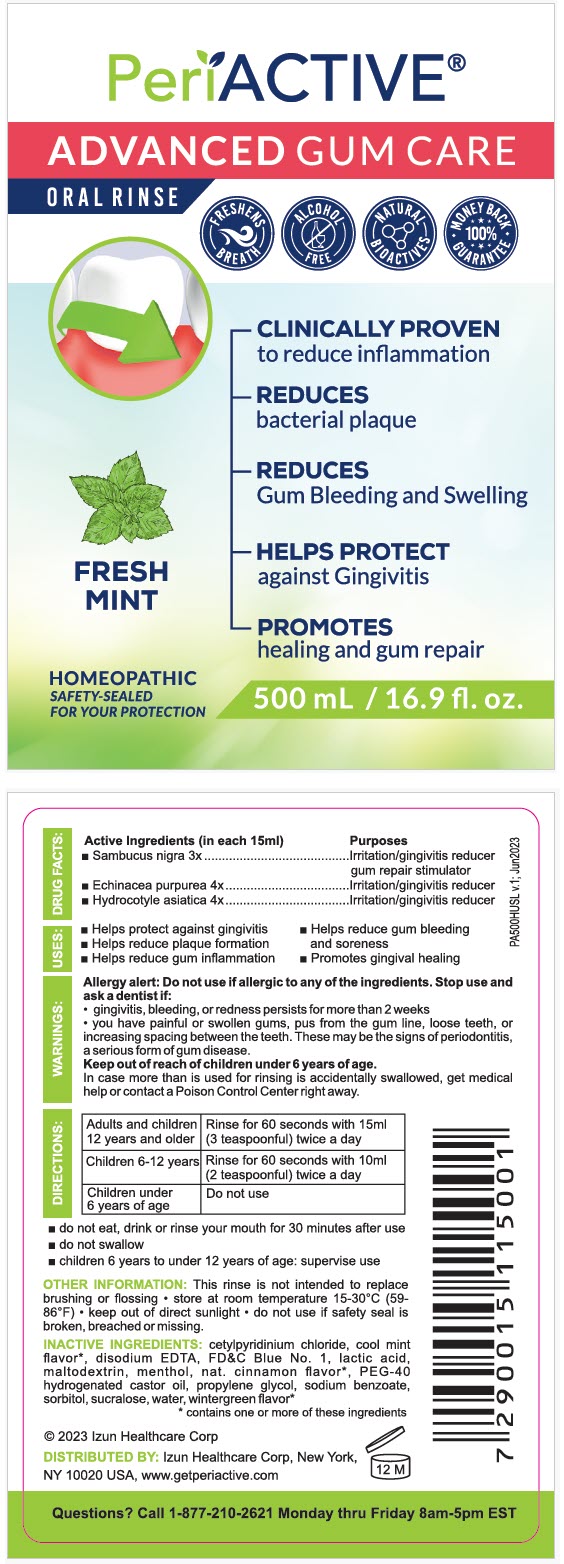 DRUG LABEL: PeriActive
NDC: 49589-111 | Form: MOUTHWASH
Manufacturer: Izun Pharmaceutical Corporation
Category: homeopathic | Type: HUMAN OTC DRUG LABEL
Date: 20241108

ACTIVE INGREDIENTS: Sambucus nigra flower 3 [hp_X]/1 mL; Echinacea purpurea whole 4 [hp_X]/1 mL; Centella asiatica whole 4 [hp_X]/1 mL
INACTIVE INGREDIENTS: cetylpyridinium chloride; edetate disodium; LACTIC ACID, UNSPECIFIED FORM; maltodextrin; polyoxyl 40 hydrogenated castor oil; propylene glycol; sodium benzoate; sorbitol; sucralose; water

PeriActive®

Drug Facts:

ACTIVE INGREDIENT

PURPOSE

Active Ingredients (in each 15ml) | Purposes
- Sambucus nigra 3x | Irritation/gingivitis reducer gum repair stimulator
- Echinacea purpurea 4x | Irritation/gingivitis reducer
- Hydrocotyle asiatica 4x | Irritation/gingivitis reducer

Uses

- Helps protect against gingivitis
- Helps reduce gum bleeding and soreness
- Helps reduce plaque formation
- Helps reduce gum inflammation
- Promotes gingival healing

Warnings

Allergy alert

Do not use if allergic to any of the ingredients. Stop use and ask a dentist if:

- gingivitis, bleeding, or redness persists for more than 2 weeks
- you have painful or swollen gums, pus from the gum line, loose teeth, or increasing spacing between the teeth. These may be the signs of periodontitis, a serious form of gum disease.

Keep out of reach of children under 6 years of age.

In case more than is used for rinsing is accidentally swallowed, get medical help or contact a Poison Control Center right away.

Directions

adults and children 12 years and older | rinse for 60 seconds with 15ml (3 teaspoonful) twice a day
children 6-12 years | rinse for 60 seconds with 10ml (2 teaspoonful) twice a day
children under 6 years of age | do not use

- do not eat, drink or rinse your mouth for 30 minutes after use
- do not swallow
- children 6 years to under 12 years of age: supervise use

Other information

This rinse is not intended to replace brushing or flossing

- store at room temperature 15-30°C (59-86°F)
- keep out of direct sunlight
- do not use if safety seal is broken, breached or missing

Inactive ingredients

cetylpyridinium chloride, cool mint flavor [contains one or more of these ingredients] , disodium EDTA, FD&C Blue No. 1 ,lactic acid, maltodextrin, menthol, nat. cinnamon flavor, PEG-40 hydrogenated castor oil, propylene glycol, sodium benzoate, sorbitol, sucralose, water, wintergreen flavor

Questions?

Call 1-877-210-2621 Monday thru Friday 8am-5pm EST

DISTRIBUTED BY: Izun Healthcare Corp, New York,
NY 10020 USA

PRINCIPAL DISPLAY PANEL - 500 mL Bottle Label

PeriACTIVE®

ADVANCED GUM CARE
ORAL RINSE

FRESHENS
BREATH

ALCOHOL
FREE

NATURAL
BIOACTIVES

MONEY BACK
100%
GUARANTEE

CLINICALLY PROVEN
to reduce inflammation

REDUCES
bacterial plaque

REDUCES
Gum Bleeding and Swelling

HELPS PROTECT
against Gingivitis

PROMOTES
healing and gum repair

FRESH
MINT

HOMEOPATHIC
SAFETY-SEALED
FOR YOUR PROTECTION

500 mL / 16.9 fl. oz.